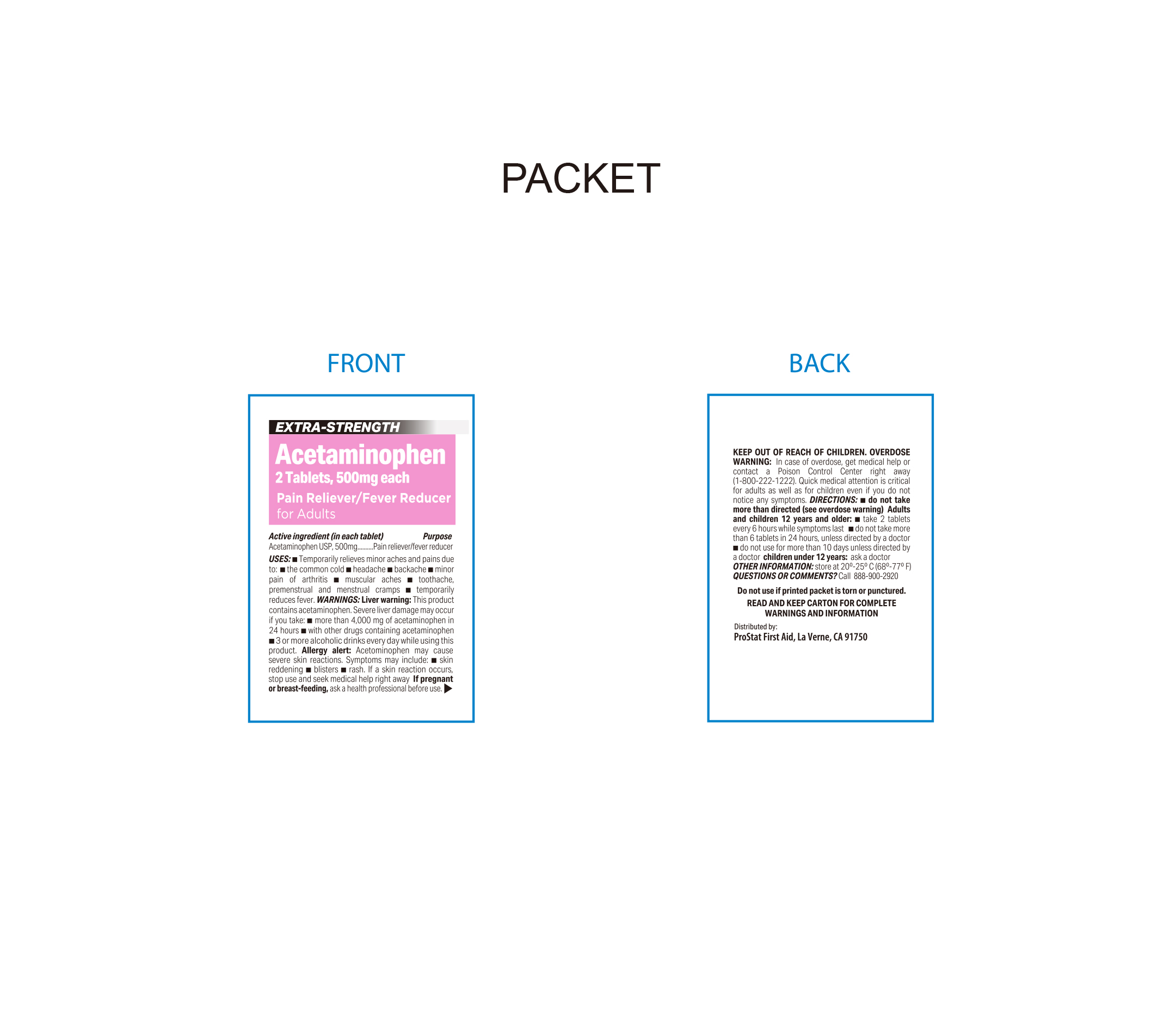 DRUG LABEL: Acetaminophen
NDC: 58228-1986 | Form: TABLET
Manufacturer: Prostat First Aid
Category: otc | Type: HUMAN OTC DRUG LABEL
Date: 20250808

ACTIVE INGREDIENTS: ACETAMINOPHEN 500 mg/1 1
INACTIVE INGREDIENTS: STEARIC ACID; POLYETHYLENE GLYCOL, UNSPECIFIED; STARCH, CORN; SODIUM STARCH GLYCOLATE TYPE A POTATO; HYPROMELLOSE, UNSPECIFIED; POVIDONE K30

PROSTAT Acetaminophen 500mg

Active Ingredient

Acetaminophen USP, 500mg (in each tablet)

Purpose

Pain Releiver / Fever Reducer

Do Not Use

With any other drug containing acetaminophen (prescription or nonprescription), if you are not sure whether a drug contains acetaminophen, ask a doctor or pharmacist.

If you are allergic to acetaminophen or any of the inactive ingredients in this product.

Uses

Temporarily relieves minor aches and pains due to

Common cold

headache

minor pain of arthritis

toothache

muscular aches

premenstrual and menstrual cramps

temporarily relieves fever

Warnings

Liver warning

This product contains acetaminophen.

Severe liver damage may occur if:

- adutls take more than 4000mg of acetaminophen in 24 hours
- child takes more than 5 doses in 24 hours, which is the maximum daily amount.
- taken with other drugs containing acetaminophen
- adult has 3 or more alcoholic drinks every day while using this product

Allergy alert

Acetaminophen may cause severe skin reactions. Symptoms may include

- skin reddening
- blisters
- rash

if a skin reaction occurs stop use ad seek medical medical help right away

Ask a doctor before use if you have

Liver Disease

Ask a doctor or pharmacist before use if you are

taking the blood thinning drug warfarin.

Keep out of reach of children, overdose warning.

In case of overdose, get medical help or contact a Poison Control Center right away. (1-800-222-1222).

Quick medical attention is critical for adults as well as for children even if you do not notice any signs or symptoms.

Directions

Do not take more than directed. (see overdose warning).

Adults and children 12 years and older

- Take 2 tablets every 6 hours while symptoms last
- Do not take more than 6 tablets in 24 hours unless directed by a doctor
- Do not use for more than 10 days unless directed by a doctor

Children under 12 years of age:

- Ask a doctor

Stop Use and ask a doctor if

- Pain gets worse or lasts more than 10 days
- fever gets worse or lasts more than 3 days
- new symptoms occur
- redness or swelling is present

These could be a sign of a serious condition

If pregnant or breast-feeding

Ask a health professional before use

Overdose Warning

In case of overdose, get medical help or contact a Poison Control Center right away (1-800-222-1222). Quick medical attention is cretical for adults as well as children even if you do not notice symptoms.

Other Information

- Store at 20ºC - 25ºC (68ºF - 77ºF)
- Do not use if printed packet is torn or punctured
- Read and keep carton for complete warnings and information

Inactive Ingredients

hydroxypropyl methyl cellulose, polyethylene glycol, povidone K-30, Pregelatinized starch, Sodium starch glycoate, Stearic Acid

Questions or Comments?

Call 1-888-900-2920

Distributed By:

ProStat First Aid

La Verne, CA. 91750 USA

*This product is not manufactured or distributed by the Johnson & Johnson Corporation, owner of the registered trademark Tylenol®

Made in the USA